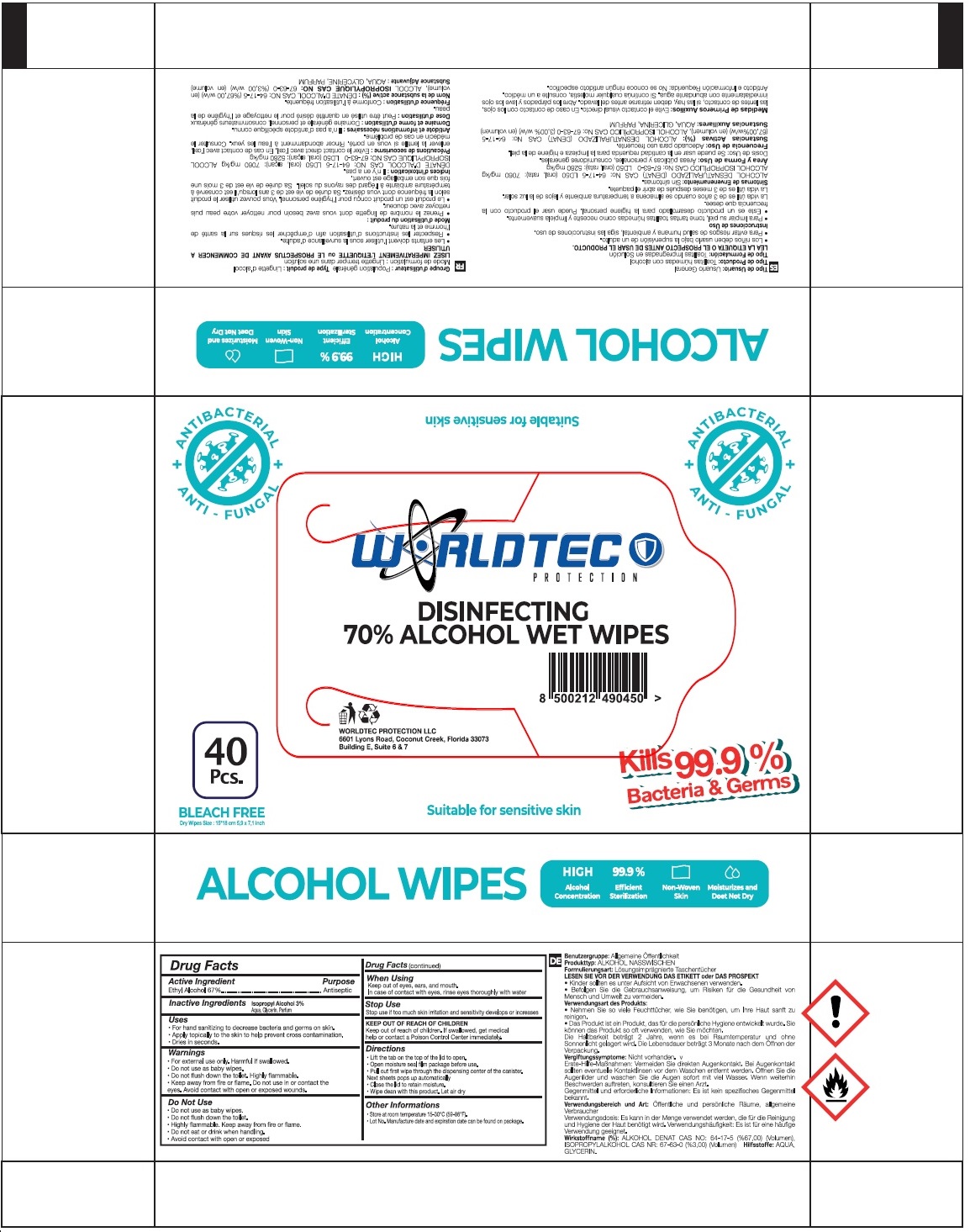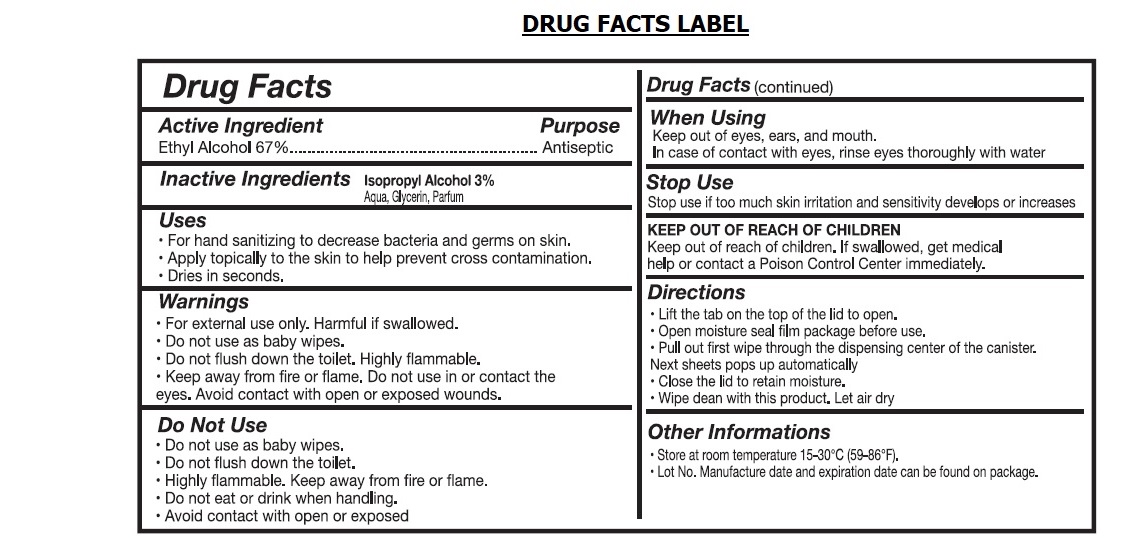 DRUG LABEL: WORLDTEC DISINFECTING 70% ALCOHOL WET WIPES
NDC: 76725-015 | Form: CLOTH
Manufacturer: MAKYAJ KOZMETIK INSAAT SANAYI VE TICARET LIMITED SIRKETI
Category: otc | Type: HUMAN OTC DRUG LABEL
Date: 20200921

ACTIVE INGREDIENTS: ALCOHOL 67 g/100 g
INACTIVE INGREDIENTS: ISOPROPYL ALCOHOL; WATER; GLYCERIN

WORLDTEC DISINFECTING 70% ALCOHOL WET WIPES

Active Ingredient

Ethyl Alcohol 67%

Purpose

Antiseptic

Inactive Ingredients Isopropyl Alcohol 3%

Aqua, Glycerin, Parfum

Uses

• For hand sanitizing to decrease bacteria and germs on skin.

• Apply topically to the skin to help prevent cross contamination.

• Dries in seconds.

Warnings

• For external use only. Harmful if swallowed.

• Do not use as baby wipes.

• Do not flush down the toilet. Highly flammable.

• Keep away from fire or flame. Do not use in or contact the eyes. Avoid contact with open or exposed wounds.

Do Not Use

• Do not use as baby wipes.

• Do not flush down the toilet.

• Highly flammable. Keep away from fire or flame.

• Do not eat or drink when handling.

• Avoid contact with open or exposed

When Using

Keep out of eyes, ears, and mouth.

In case of contact with eyes, rinse eyes thoroughly with water

Stop Use

Stop use if too much skin irritation and sensitivity develops or increases

Keep out of reach of children. If swallowed, get medical help or contact a Poison Control Center immediately.

Directions

• Lift the tab on top of the lid to open.

• Open moisture seal film package before use.

• Pull out first wipe through the dispensing center of the canister.

Next sheets pops up automatically

• Close the lid to retain moisture.

• Wipe clean with this product. Let air dry

Other Informations

• Store at room temperature 15-30°C (59-86°F).

• Lot No. Manufacture date and expiration date can be found on package.

ANTIBACTERIAL

ANTI - FUNGAL

BLEACH FREE

Kills 99.9% Bacteria & Germs

Suitable for sensitive skin

WORLDTEC PROTECTION LLC

6601 Lyons Road, Coconut Creek,

Florida 33073 Building E, Suite 6 & 7

HIGH Alcohol Concentration

99.9% Efficient sterilization

Non-Woven Skin

Moisturizes and Does Not Dry